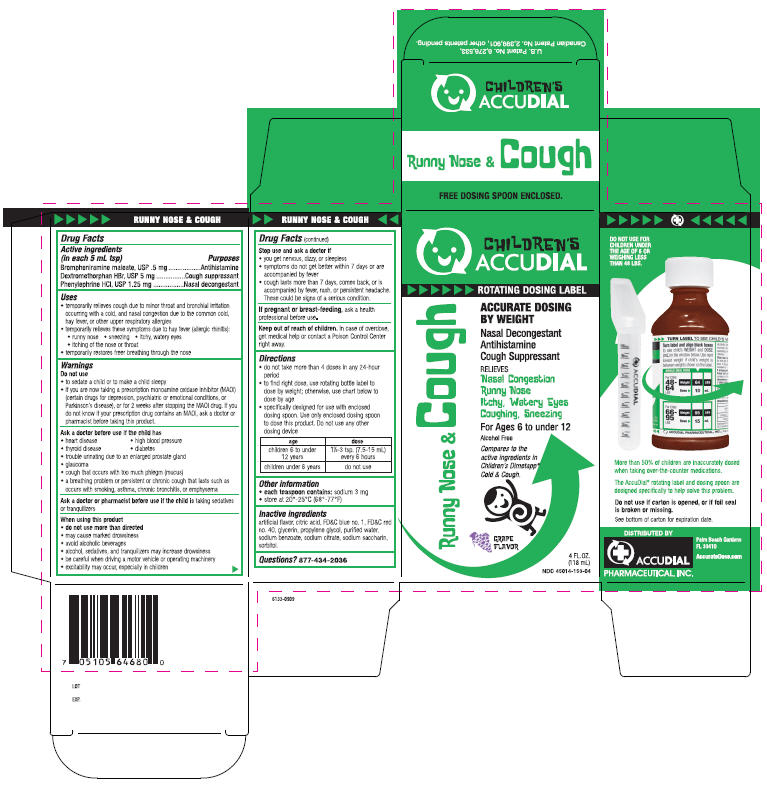 DRUG LABEL: Runny Nose and Cough
NDC: 45014-153 | Form: LIQUID
Manufacturer: Accudial Pharmaceutical, Inc.
Category: otc | Type: HUMAN OTC DRUG LABEL
Date: 20091104

ACTIVE INGREDIENTS: Brompheniramine Maleate 0.5 mg/5 mL; Dextromethorphan Hydrobromide 5 mg/5 mL; Phenylephrine Hydrochloride 1.25 mg/5 mL
INACTIVE INGREDIENTS: Grape; Citric Acid Monohydrate; FD&C Blue No. 1; FD&C Red No. 40; Glycerin; Propylene Glycol; Water; Sodium Benzoate; Sodium Citrate; Saccharin Sodium ; Sorbitol

Children's
ACCUDIAL

RUNNY NOSE & COUGH

Drug Facts

ACTIVE INGREDIENT

PURPOSE

Active ingredients (in each 5 mL tsp) | Purposes
Brompheniramine maleate, USP .5 mg | Antihistamine
Dextromethorphan HBr, USP 5 mg | Cough suppressant
Phenylephrine HCl, USP 1.25 mg | Nasal decongestant

Uses

- temporarily relieves cough due to minor throat and bronchial irritation occurring with a cold, and nasal congestion due to the common cold, hay fever, or other upper respiratory allergies
- temporarily relieves these symptoms due to hay fever (allergic rhinitis):
  - runny nose
  - sneezing
  - itchy, watery eyes
  - itching of the nose or throat
- temporarily restores freer breathing through the nose

Warnings

Do not use

- to sedate a child or to make a child sleepy
- if you are now taking a prescription monoamine oxidase inhibitor (MAOI) (certain drugs for depression, psychiatric or emotional conditions, or Parkinson's disease), or for 2 weeks after stopping the MAOI drug. If you do not know if your prescription drug contains an MAOI, ask a doctor or pharmacist before taking this product.

Ask a doctor before use if the child has

- heart disease
- high blood pressure
- thyroid disease
- diabetes
- trouble urinating due to an enlarged prostate gland
- glaucoma
- cough that occurs with too much phlegm (mucus)
- a breathing problem or persistent or chronic cough that lasts such as occurs with smoking, asthma, chronic bronchitis, or emphysema

Ask a doctor or pharmacist before use if the child is taking sedatives or tranquilizers

When using this product

- do not use more than directed
- may cause marked drowsiness
- avoid alcoholic beverages
- alcohol, sedatives, and tranquilizers may increase drowsiness
- be careful when driving a motor vehicle or operating machinery
- excitability may occur, especially in children

Stop use and ask a doctor if

- you get nervous, dizzy, or sleepless
- symptoms do not get better within 7 days or are accompanied by fever
- cough lasts more than 7 days, comes back, or is accompanied by fever, rash, or persistent headache. These could be signs of a serious condition.

PREGNANCY OR BREAST FEEDING

If pregnant or breast-feeding, ask a health professional before use.

Keep out of reach of children. In case of overdose, get medical help or contact a Poison Control Center right away.

Directions

- do not take more than 4 doses in any 24-hour period
- to find right dose, use rotating bottle label to dose by weight; otherwise, use chart below to dose by age
- specifically designed for use with enclosed dosing spoon. Use only enclosed dosing spoon to dose this product. Do not use any other dosing device

age | dose
children 6 to under 12 years | 1½-3 tsp. (7.5-15 mL) every 6 hours
children under 6 years | do not use

Other information

- each teaspoon contains: sodium 3 mg
- store at 20°-25°C (68°-77°F)

Inactive ingredients

artificial flavor, citric acid, FD&C blue no. 1, FD&C red no. 40, glycerin, propylene glycol, purified water, sodium benzoate, sodium citrate, sodium saccharin, sorbitol.

Questions?

877-434-2036

PRINCIPAL DISPLAY PANEL - 118 mL Carton

CHILDREN'S
ACCUDIAL

ROTATING DOSING LABEL

ACCURATE DOSING
BY WEIGHT

Nasal Decongestant
Antihistamine
Cough Suppressant

RELIEVES
Nasal Congestion
Runny Nose
Itchy, Watery Eyes
Coughing, Sneezing

For Ages 6 to under 12

Alcohol Free
Compares to the
active ingredients in
Children's Dimetapp®
Cold & Cough.

GRAPE
FLAVOR

4 FL. OZ.
(118 mL)
NDC 45014-153-04

Runny Nose & Cough